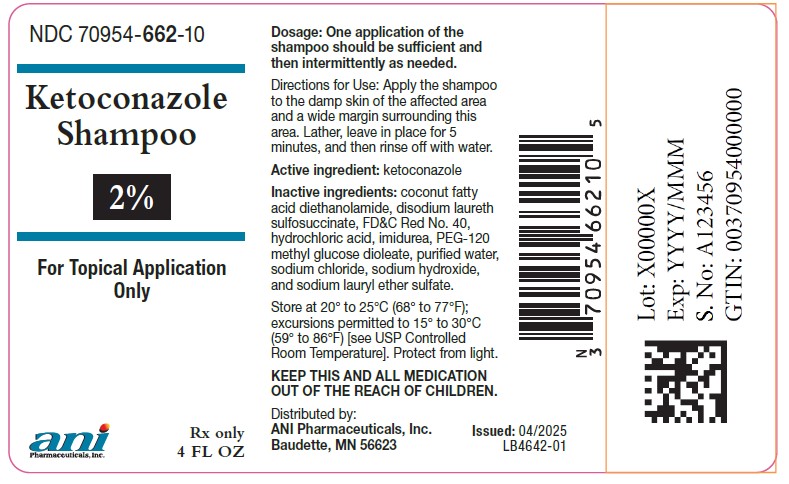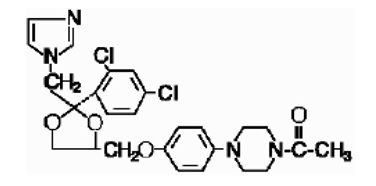 DRUG LABEL: Ketoconazole
NDC: 70954-662 | Form: SHAMPOO
Manufacturer: ANI Pharmaceuticals, Inc.
Category: prescription | Type: Human Prescription Drug Label
Date: 20260129

ACTIVE INGREDIENTS: KETOCONAZOLE 20 mg/1 mL
INACTIVE INGREDIENTS: COCO DIETHANOLAMIDE; DISODIUM LAURETH SULFOSUCCINATE; FD&C RED NO. 40; HYDROCHLORIC ACID; IMIDUREA; PEG-120 METHYL GLUCOSE DIOLEATE; WATER; SODIUM CHLORIDE; SODIUM HYDROXIDE; SODIUM LAURETH-3 SULFATE

Ketoconazole Shampoo, 2%
Rx Only

DESCRIPTION

Ketoconazole Shampoo, 2% is a red-orange color liquid for topical application, containing the broad spectrum synthetic antifungal agent ketoconazole in a concentration of 2% in an aqueous suspension. It also contains: coconut fatty acid diethanolamide, disodium laureth sulfosuccinate, FD&C Red No. 40, hydrochloric acid, imidurea, PEG-120 methyl glucose dioleate, purified water, sodium chloride, sodium hydroxide, and sodium lauryl ether sulfate.

Ketoconazole is cis-1-acetyl-4-[4-[[2-(2,4-dichlorophenyl)-2-(1H-imidazol-1-ylmethyl)-1,3-dioxolan-4-yl]methoxy]phenyl]piperazine and has the following structural formula:

CLINICAL PHARMACOLOGY

Tinea (pityriasis) versicolor is a non-contagious infection of the skin caused by Pityrosporum orbiculare (Malassezia furfur). This commensal organism is part of the normal skin flora. In susceptible individuals the condition is often recurrent and may give rise to hyperpigmented or hypopigmented patches on the trunk which may extend to the neck, arms and upper thighs. Treatment of the infection may not immediately result in restoration of pigment to the affected sites. Normalization of pigment following successful therapy is variable and may take months, depending on individual skin type and incidental skin exposure. The rate of recurrence of infection is variable.

Ketoconazole was not detected in plasma in 39 patients who shampooed 4-10 times per week for 6 months, or in 33 patients who shampooed 2-3 times per week for 3-26 months (mean: 16 months).

An exaggerated use washing test on the sensitive antecubital skin of 10 subjects twice daily for five consecutive days showed that the irritancy potential of ketoconazole shampoo, 2% was significantly less than that of 2.5% selenium sulfide shampoo.

A human sensitization test, a phototoxicity study, and a photoallergy study conducted in 38 male and 22 female volunteers showed no contact sensitization of the delayed hypersensitivity type, no phototoxicity and no photoallergenic potential due to ketoconazole shampoo, 2%.

Mode of Action: Interpretations of in vivo studies suggest that ketoconazole impairs the synthesis of ergosterol, which is a vital component of fungal cell membranes. It is postulated, but not proven, that the therapeutic effect of ketoconazole in tinea (pityriasis) versicolor is due to the reduction of Pityrosporum orbiculare (Malassezia furfur) and that the therapeutic effect in dandruff is due to the reduction of Pityrosporum ovale. Support for the therapeutic effect in tinea versicolor comes from a three-arm, parallel, double-blind, placebo controlled study in patients who had moderately severe tinea (pityriasis) versicolor. Successful response rates in the primary efficacy population for each of both three-day and single-day regimens of ketoconazole shampoo, 2% were statistically significantly greater (73% and 69%, respectively) than a placebo regimen (5%). There had been mycological confirmation of fungal disease in all cases at baseline. Mycological clearing rates were 84% and 78%, respectively, for the three-day and one-day regimens of the 2% shampoo and 11% in the placebo regimen. While the differences in the rates of successful response between either of the two active treatments and placebo were statistically significant, the difference between the two active regimens was not.

Microbiology: Ketoconazole is a broad spectrum synthetic antifungal agent which inhibits the growth of the following common dermatophytes and yeasts by altering the permeability of the cell membrane: dermatophytes: Trichophyton rubrum, T. mentagrophytes, T. tonsurans, Microsporum canis, M. audouini, M. gypseum and Epidermophyton floccosum; yeasts: Candida albicans, C. tropicalis, Pityrosporum ovale (Malassezia ovale) and Pityrosporum orbiculare (M. furfur). Development of resistance by these microorganisms to ketoconazole has not been reported.

INDICATIONS & USAGE

Ketoconazole shampoo, 2% is indicated for the treatment of tinea (pityriasis) versicolor caused by or presumed to be caused by Pityrosporum orbiculare (also known as Malassezia furfur or M. orbiculare).

Note: Tinea (pityriasis) versicolor may give rise to hyperpigmented or hypopigmented patches on the trunk which may extend to the neck, arms and upper thighs. Treatment of the infection may not immediately result in normalization of pigment to the affected sites. Normalization of pigment following successful therapy is variable and may take months, depending on individual skin type and incidental sun exposure. Although tinea versicolor is not contagious, it may recur because the organism that causes the disease is part of the normal skin flora.

CONTRAINDICATIONS

Ketoconazole shampoo, 2% is contraindicated in persons who have known hypersensitivity to the active ingredient or excipients of this formulation.

PRECAUTIONS

Severe hypersensitivity reactions, including anaphylaxis, have been reported during post-marketing use of ketoconazole shampoo. If a reaction suggesting sensitivity or chemical irritation should occur, use of the medication should be discontinued.

INFORMATION FOR PATIENTS

Patients should be advised of the following:

- Ketoconazole shampoo, 2% may be irritating to mucous membranes of the eyes and contact with this area should be avoided.
- The following have been reported with the use of ketoconazole shampoo, 2%: hair discoloration and abnormal hair texture, removal of the curl from permanently waved hair, itching, skin burning sensation and contact dermatitis, hypersensitivity, angioedema, alopecia, rash, urticaria, skin irritation, dry skin, and application site reactions.
- Patients who develop allergic reactions, such as generalized rash, skin reactions, severe swelling, angioedema, or shortness of breath should discontinue ketoconazole shampoo, 2% and contact their physician immediately.

CARCINOGENESIS & MUTAGENESIS & IMPAIRMENT OF FERTILITY

Long-term studies to assess the carcinogenic potential of ketoconazole shampoo, 2% have not been conducted. A long-term feeding study of ketoconazole in Swiss Albino mice and in Wistar rats showed no evidence of oncogenic activity. The dominant lethal mutation test in male and female mice revealed that single oral doses of ketoconazole as high as 80 mg/kg were not genotoxic. The Ames Salmonella microsomal activator assay was also negative.

PREGNANCY

Teratogenic effects: Pregnancy Category C:

There are no adequate and well-controlled studies in pregnant women. Ketoconazole should be used during pregnancy only if the potential benefit justifies the potential risk to the fetus. In humans, ketoconazole is not detected in plasma after chronic shampooing on the scalp.

Ketoconazole has been shown to be teratogenic (syndactylia and oligodactylia) in the rat when given orally in the diet at 80 mg/kg/day (a dose 10 times the maximum recommended human oral dose). However, these effects may be related to maternal toxicity, which was seen at this and higher dose levels.

NURSING MOTHERS

There are no adequate and well-controlled studies in nursing women. Ketoconazole is not detected in plasma after chronic shampooing on the scalp. Caution should be exercised when ketoconazole shampoo, 2% is administered to a nursing woman.

PEDIATRIC USE

Safety and effectiveness in children have not been established.

ADVERSE REACTIONS

Clinical Trials Experience

In 11 double-blind trials in 264 patients using ketoconazole shampoo, 2% for the treatment of dandruff or seborrheic dermatitis, an increase in normal hair loss and irritation occurred in less than 1% of patients. In three open label safety trials in which 41 patients shampooed 4-10 times weekly for six months, the following adverse experiences each occurred once: abnormal hair texture, scalp pustules, mild dryness of the skin, and itching. As with other shampoos, oiliness and dryness of hair and scalp have been reported. In a double-blind, placebo-controlled trial in which patients with tinea versicolor were treated with either a single application of ketoconazole shampoo, 2% (n=106), a daily application for three consecutive days (n=107), or placebo (n=105), drug-related adverse events occurred in 5 (5%), 7 (7%) and 4 (4%) of patients, respectively. The only events that occurred in more than one patient in any one of the three treatment groups were pruritus, application site reaction, and dry skin; none of these events occurred in more than 3% of the patients in any one of the three groups.

Post-marketing Experience

Because these reactions are reported voluntarily from a population of uncertain size, it is not possible to reliably estimate their frequency. The following adverse drug reactions have been identified during post-marketing experience with ketoconazole shampoo: there have been reports of hair discoloration and abnormal hair texture, itching, skin burning sensation, contact dermatitis, hypersensitivity, angioedema, alopecia, rash, urticaria, skin irritation, dry skin, and application site reactions.

OVERDOSAGE

Ketoconazole shampoo, 2% is intended for external use only. In the event of accidental ingestion, supportive and symptomatic measures should be employed. Induced emesis and gastric lavage should not be performed to avoid aspiration.

DOSAGE & ADMINISTRATION

Apply the shampoo to the damp skin of the affected area and a wide margin surrounding this area. Lather, leave in place for 5 minutes, and then rinse off with water.

One application of the shampoo should be sufficient.

HOW SUPPLIED

Ketoconazole Shampoo, 2% is a red-orange color liquid supplied in a 4-fluid ounce (120 mL) non-breakable plastic bottle (NDC 70954-662-10).

Storage conditions: Store at 20° to 25°C (68° to 77°F); excursions permitted to 15° to 30°C (59° to 86°F) [see USP Controlled Room Temperature]. Protect from light.

All trademarks are the property of their respective owners.

Distributed by:

ANI Pharmaceuticals, Inc.

Baudette, MN 56623

Issued: 07/2024

LB4643-01

PACKAGE LABEL.PRINCIPAL DISPLAY PANEL

Ketoconazole Shampoo, 2% - NDC 70954-662-10 - 120 mL per bottle